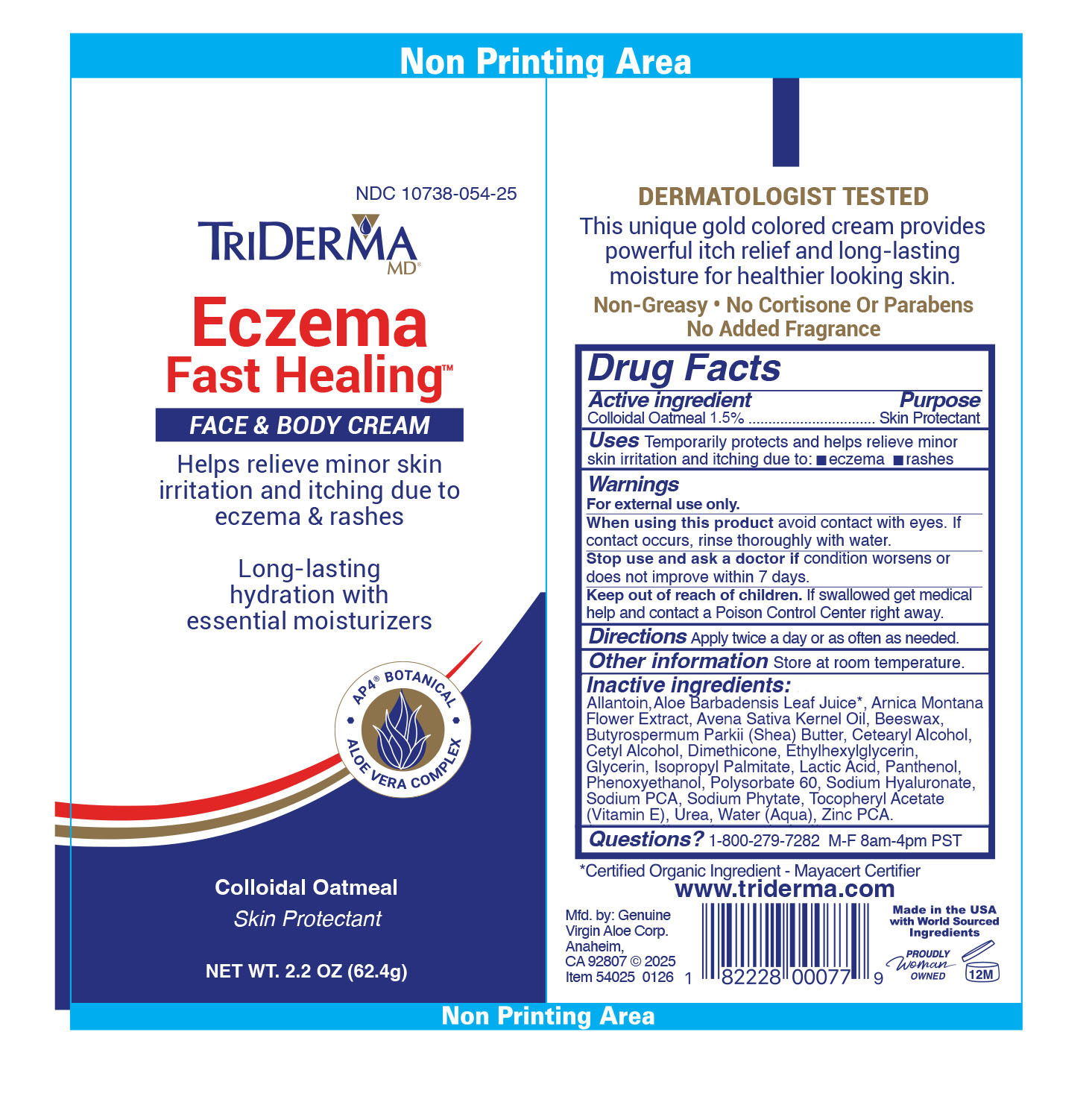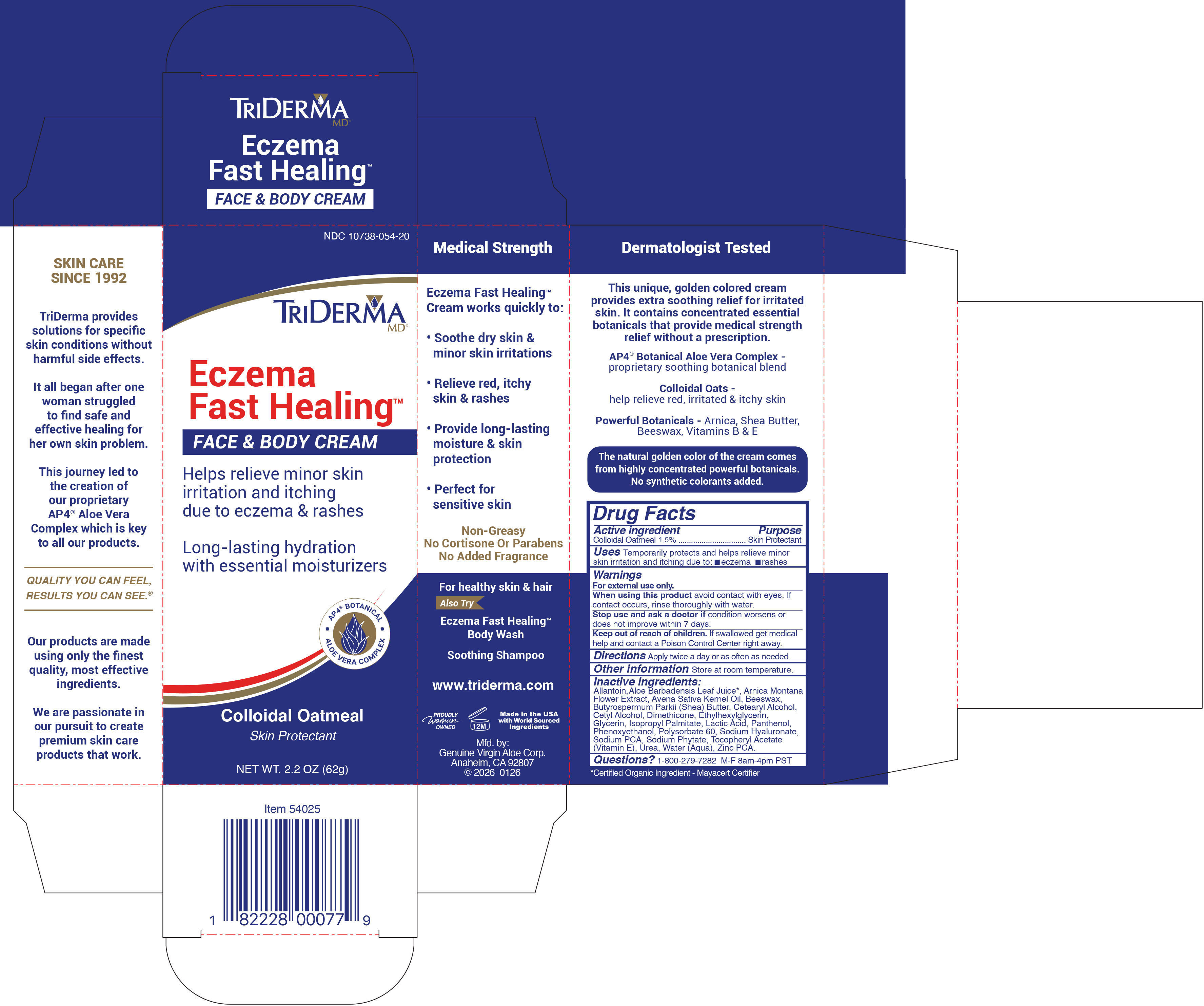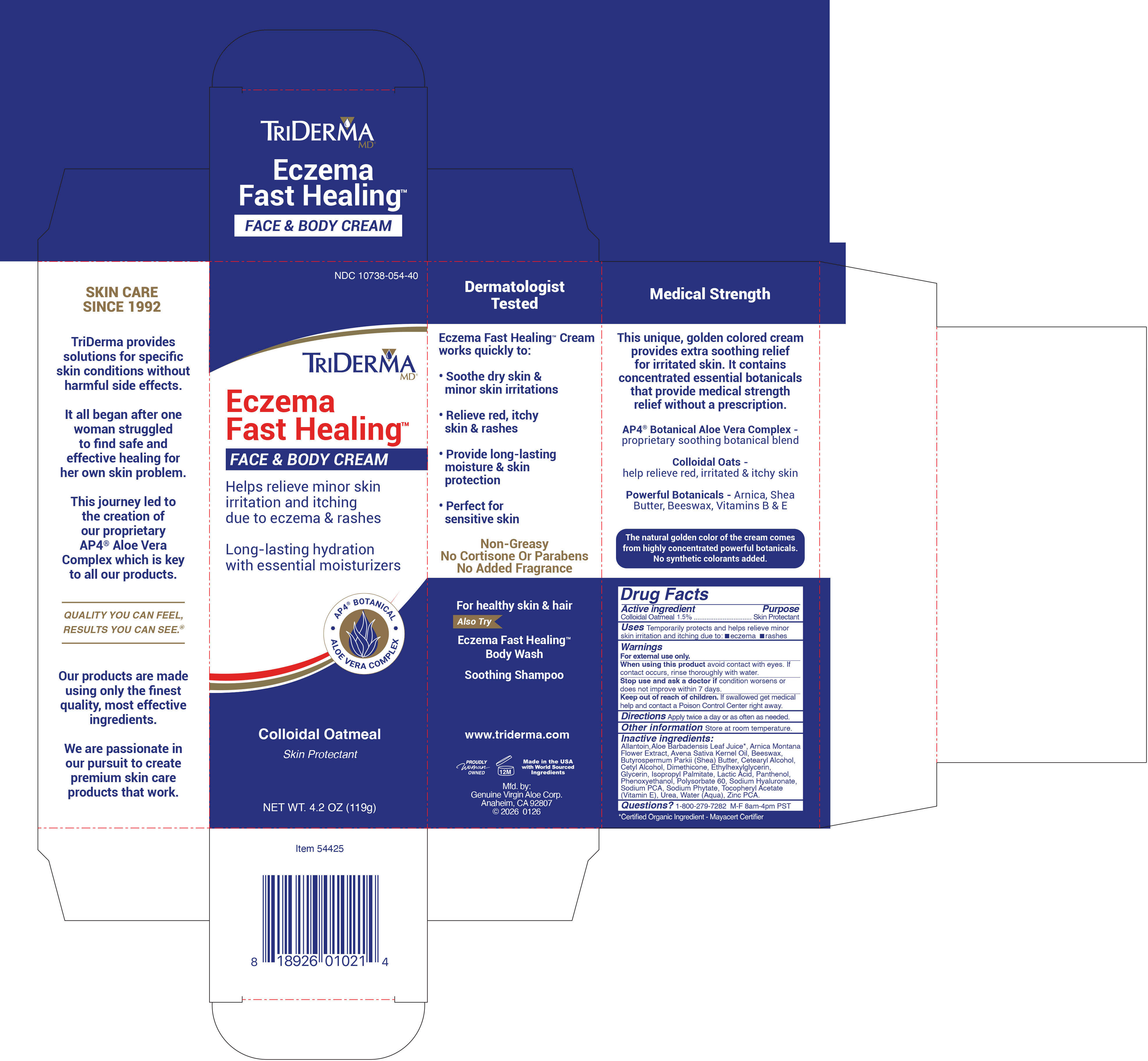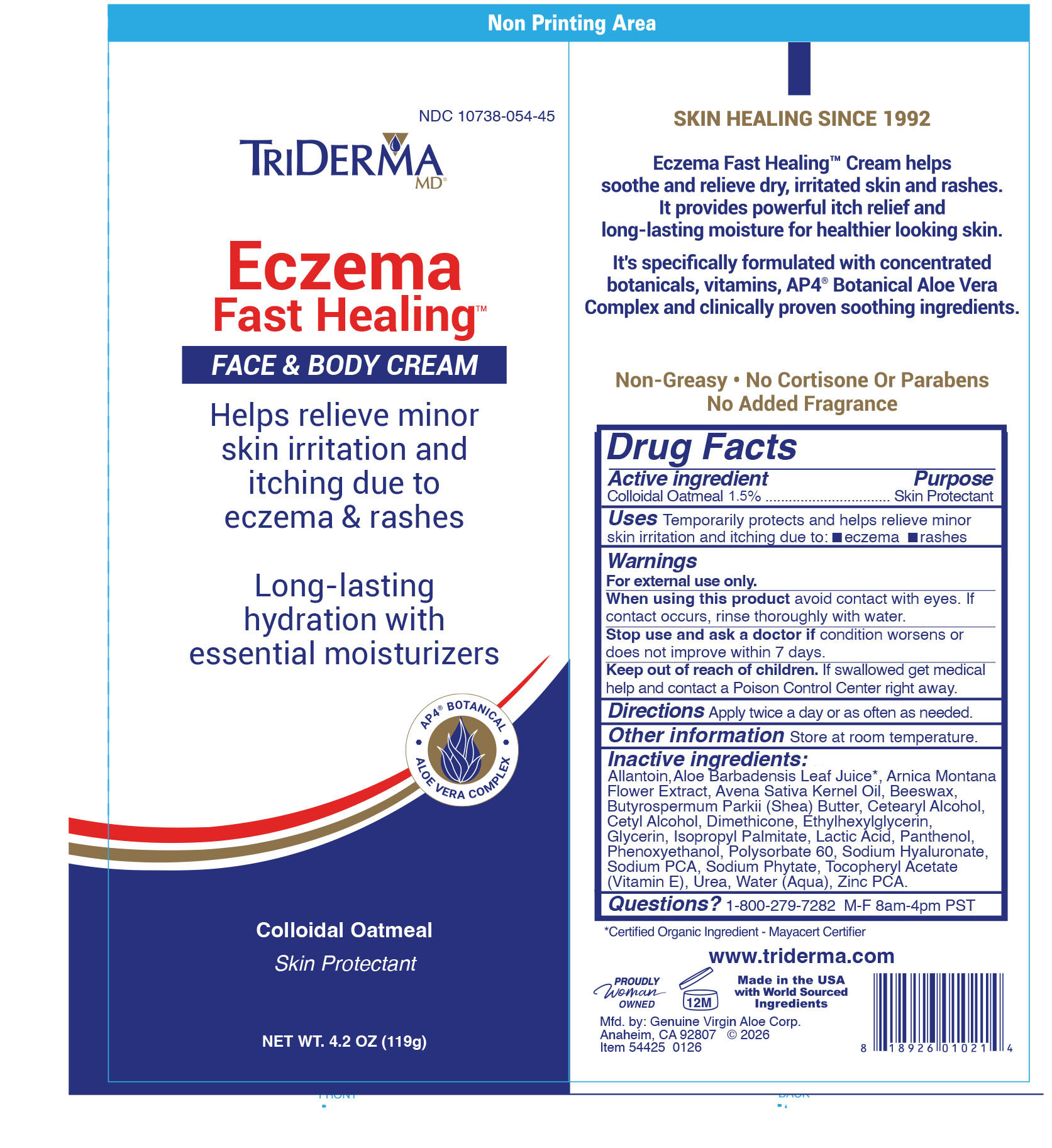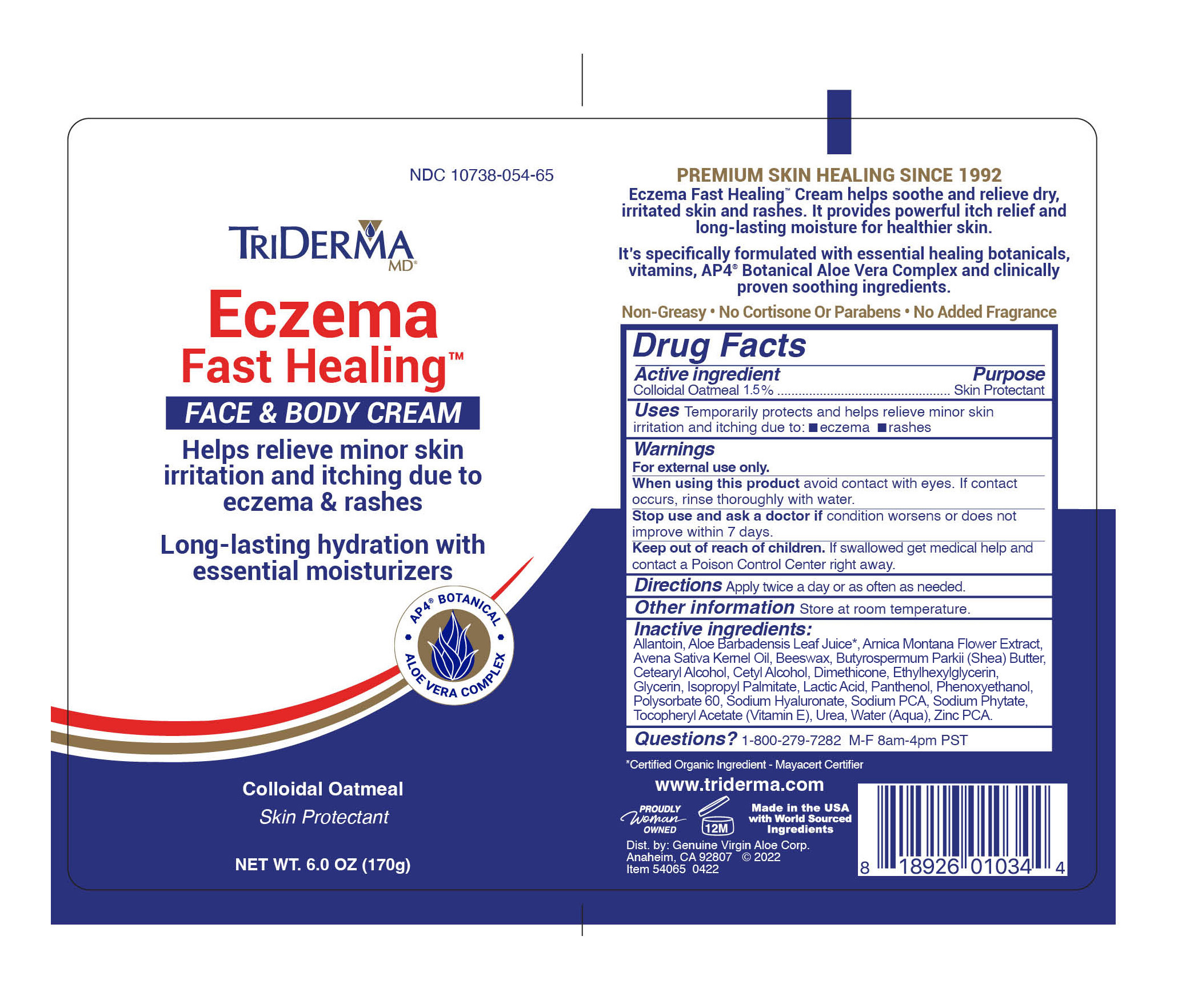 DRUG LABEL: TRIDERMA ECZEMA FAST HEALING FACE AND BODY
NDC: 10738-054 | Form: CREAM
Manufacturer: Genuine Virgin Aloe Corporation
Category: otc | Type: HUMAN OTC DRUG LABEL
Date: 20260129

ACTIVE INGREDIENTS: OATMEAL 1.5 g/100 g
INACTIVE INGREDIENTS: AVENA SATIVA (OAT) KERNEL OIL; SODIUM PCA; WATER; CETOSTEARYL ALCOHOL; UREA; ISOPROPYL PALMITATE; ARNICA MONTANA FLOWER; GLYCERIN; POLYSORBATE 60; BEESWAX; DIMETHICONE; ALLANTOIN; ZINC PCA; ALOE VERA LEAF; PANTHENOL; SHEA BUTTER; .ALPHA.-TOCOPHEROL ACETATE; HYALURONATE SODIUM; CETYL ALCOHOL; PHYTATE SODIUM; LACTIC ACID; PHENOXYETHANOL; ETHYLHEXYLGLYCERIN

TRIDERMA ECZEMA FAST HEALING FACE & BODY CREAM

Active ingredient

Colloidal oatmeal 1.5%

Purpose

Skin protectant

INDICATIONS AND USAGE

Uses temporarily protects and helps relieve minor skin irritation and itching due to: •eczema •rashes

Warnings For external use only.

Do not use •on deep puncture wounds •on infections •on lacerations

When using this product •do not get into eyes

Stop use and ask a doctor if •condition worsens or does not improve within 7 days

Keep out of reach of children.
If swallowed get medical help or contact a Poison Control Center right away.

DOSAGE AND ADMINISTRATION

Directions •apply twice a day or as needed.

Other Information •store at room temperature.

INACTIVE INGREDIENT

Inactive ingredients: Allantoin, Aloe Barbadensis Leaf Juice*, Arnica Montana Flower Extract, Avena Sativa Kernel Oil, Butyrospermum Parkii (Shea) Butter, Cera Alba (Beeswax), Cetearyl Alcohol, Cetyl Alcohol, Dimethicone, Ethylhexylglycerin, Glycerin, Isopropyl Palmitate, Lactic Acid, Panthenol (Pro-Vitamin B5), Phenoxyethanol, Polysorbate 60, Sodium Hyaluronate, Sodium PCA, Sodium Phytate, Tocopheryl Acetate (Vitamin E), Urea, Water, Zinc PCA
*Certified Organic Ingredient - Mayacert Certifier

QUESTIONS

Questions? 1-800-279-7282 M-F 8am-4pm PST

Temporarily protects & helps relieve minor skin irritation due to eczema & rashes
Helps relieve itching

AP4 BOTANICAL

ALOE VERA COMPLEX

with Colloidal Oatmeal

Maximum Strength
Healing Botanicals

Eczema Fast Healing™ cream helps promote fast relief for itching and rashes due to Eczema related symptoms.
This rich cream contains essential healing botanicals, vitamins and AP4® Aloe Vera Complex. It provides long lasting moisture and helps relieve itching without harmful drugs.

Non-Greasy
No Added Fragrance or Parabens

Mfd by: Genuine Virgin Aloe Corp.,

Anaheim, CA 92807

•AP4® Aloe Vera Complex, a proprietary botanical blend

• Colloidal Oatmeal, helps relieve skin irritations due to Eczema and rashes

• Shea Butter, Arnica Montana Flower & Beeswax

• Vitamins B and E

Rooted from a medical heritage, TriDerma MD® was founded after one woman’s struggle to find safe and effective skin healing.
At TriDerma MD®, we strive to create the perfect formulations for specific skin irritations. Our products are made using only the finest quality, most effective ingredients. We are passionate in our pursuit of fast healing, natural botanicals that do not cause harmful side effects.

Quality you can feel, results you can see. ®